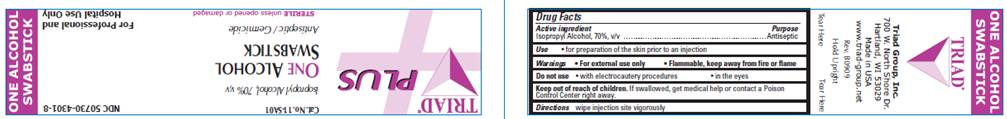 DRUG LABEL: Isopropyl alcohol Swabstick Sterile
NDC: 50730-4301 | Form: LIQUID
Manufacturer: H and P Industries, Inc. dba Triad Group
Category: otc | Type: HUMAN OTC DRUG LABEL
Date: 20100126

ACTIVE INGREDIENTS: Isopropyl alcohol 0.7 mL/1 mL
INACTIVE INGREDIENTS: water

DRUG FACTS

ACTIVE INGREDIENT

Isopropyl Alcohol 70% v/v

PURPOSE

Antiseptic

USE

- For preparation of the skin prior to injection

WARNINGS

- For external use only

- Flammable, keep away from fire or flame

Do not use

- With electrocautery procedures
- In the eyes

KEEP OUT OF REACH OF CHILDREN

If swallowed, get medical help or contact a Poison Control Center right away.

DIRECTIONS

Wipe injection site vigorously and discard.

INACTIVE INGREDIENT

purified water

PACKAGE INFORMATION

TRIAD
PLUS
Cat No. 11-SA01
NDC 50730-4301-8
Isopropyl alcohol, 70% v/v
ONE ALCOHOL
SWABSTICK
Antiseptic / Germicide
Sterile unless opened or damaged
for Professional and Hospital Use Only
Triad Group, Inc.
700 W. North Shore Dr.
Hartland, WI 53029
Made in USA
www.triad-group.net
Rev. B0909
Hold Upright
Tear Here